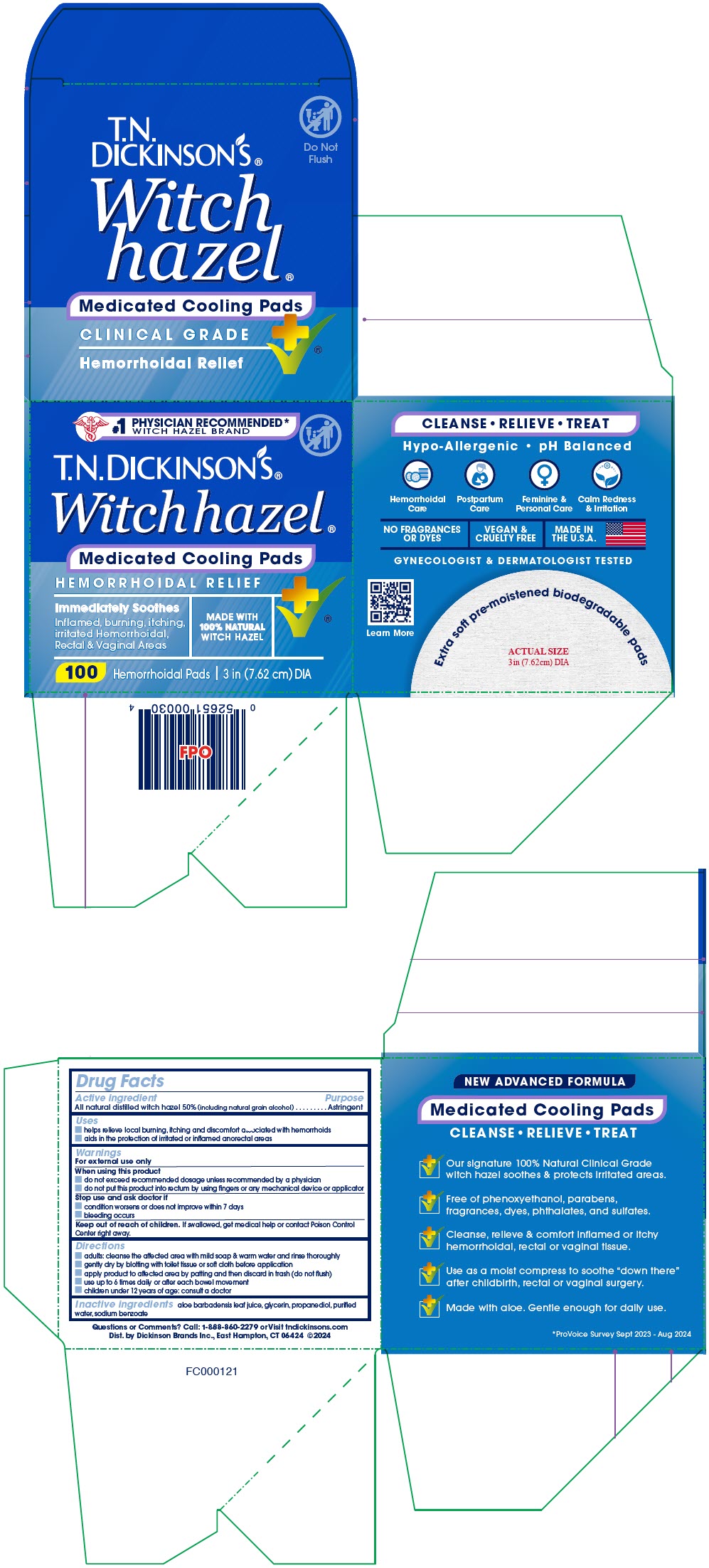 DRUG LABEL: T.N. Dickinsons Witch Hazel Medicated Cooling Pads Hemorrhoidal Relief
NDC: 52651-010 | Form: CLOTH
Manufacturer: Dickinson Brands Inc.
Category: otc | Type: HUMAN OTC DRUG LABEL
Date: 20241212

ACTIVE INGREDIENTS: WITCH HAZEL 0.034 g/1 1
INACTIVE INGREDIENTS: WATER; GLYCERIN; PROPANEDIOL; SODIUM BENZOATE; ALOE VERA LEAF

T.N. Dickinson's® Witch Hazel® Medicated Cooling Pads Hemorrhoidal Relief

Drug Facts

Active ingredient

All natural distilled witch hazel 50% (including natural grain alcohol)

Purpose

Astringent

Uses

- helps relieve local burning, itching and discomfort associated with hemorrhoids
- aids in the protection of irritated or inflamed anorectal areas

Warnings

For external use only

When using this product

- do not exceed recommended dosage unless recommended by a physician
- do not put this product into rectum by using fingers or any mechanical device or applicator

Stop use and ask doctor if

- condition worsens or does not improve within 7 days
- bleeding occurs

Keep out of reach of children. If swallowed, get medical help or contact Poison Control Center right away.

Directions

- adults: cleanse the affected area with mild soap & warm water and rinse thoroughly
- gently dry by blotting with toilet tissue or soft cloth before application
- apply product to affected area by patting and then discard in trash (do not flush)
- use up to 6 times daily or after each bowel movement
- children under 12 years of age: consult a doctor

Inactive ingredients

aloe barbadensis leaf juice, glycerin, propanediol, purified water, sodium benzoate

Questions or Comments?

Call: 1-888-860-2279 or Visit tndickinsons.com

Dist. by Dickinson Brands Inc., East Hampton, CT 06424

PRINCIPAL DISPLAY PANEL - 100 Pad Jar Carton

#1
PHYSICIAN RECOMMENDED*
WITCH HAZEL BRAND

T.N. Dickinson's®
Witch hazel®

Medicated Cooling Pads

HEMORRHOIDAL RELIEF

Immediately Soothes
Inflamed, burning, itching,
irritated Hemorrhoidal,
Rectal & Vaginal Areas

MADE WITH
100% NATURAL
WITCH HAZEL

100 Hemorrhoidal Pads | 3 in (7.62 cm) DIA